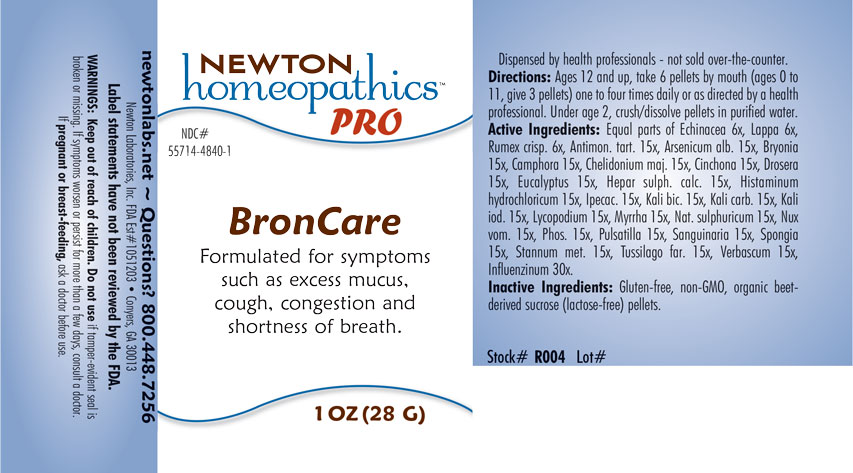 DRUG LABEL: BronCare
NDC: 55714-4840 | Form: PELLET
Manufacturer: Newton Laboratories, Inc.
Category: otc | Type: HUMAN OTC DRUG LABEL
Date: 20200518

ACTIVE INGREDIENTS: CINCHONA OFFICINALIS BARK 15 [hp_X]/1 g; CALCIUM SULFIDE 15 [hp_X]/1 g; HISTAMINE DIHYDROCHLORIDE 15 [hp_X]/1 g; IPECAC 15 [hp_X]/1 g; ARCTIUM LAPPA ROOT 6 [hp_X]/1 g; ANEMONE PULSATILLA 15 [hp_X]/1 g; DROSERA ANGLICA 15 [hp_X]/1 g; LYCOPODIUM CLAVATUM SPORE 15 [hp_X]/1 g; PHOSPHORUS 15 [hp_X]/1 g; VERBASCUM THAPSUS 15 [hp_X]/1 g; POTASSIUM DICHROMATE 15 [hp_X]/1 g; SODIUM SULFATE 15 [hp_X]/1 g; BRYONIA ALBA ROOT 15 [hp_X]/1 g; SPONGIA OFFICINALIS SKELETON, ROASTED 15 [hp_X]/1 g; TUSSILAGO FARFARA 15 [hp_X]/1 g; CHELIDONIUM MAJUS 15 [hp_X]/1 g; TIN 15 [hp_X]/1 g; INFLUENZA B VIRUS 30 [hp_X]/1 g; STRYCHNOS NUX-VOMICA SEED 15 [hp_X]/1 g; SANGUINARIA CANADENSIS ROOT 15 [hp_X]/1 g; INFLUENZA A VIRUS 30 [hp_X]/1 g; RUMEX CRISPUS ROOT 6 [hp_X]/1 g; ANTIMONY POTASSIUM TARTRATE 15 [hp_X]/1 g; POTASSIUM IODIDE 15 [hp_X]/1 g; ARSENIC TRIOXIDE 15 [hp_X]/1 g; CAMPHOR (NATURAL) 15 [hp_X]/1 g; ECHINACEA, UNSPECIFIED 6 [hp_X]/1 g; POTASSIUM CARBONATE 15 [hp_X]/1 g; MYRRH 15 [hp_X]/1 g
INACTIVE INGREDIENTS: SUCROSE

BronCare 4840P

INDICATIONS & USAGE SECTION

Formulated for symptoms such as excess mucus, cough, congestion and shortness of breath.

DOSAGE & ADMINISTRATION SECTION

Directions: Ages 12 and up, take 6 pellets by mouth (ages 0 to 11, give 3 pellets) one to four times daily or as directed by a health professional. Under age 2, crush/dissolve pellets in purified water.

OTC - ACTIVE INGREDIENT SECTION

Equal parts of Echinacea 6x, Lappa 6x, Rumex crisp. 6x, Antimon. tart. 15x, Arsenicum alb. 15x, Bryonia 15x, Camphora 15x, Chelidonium maj. 13x, Cinchona 13x, Drosera 13x, Eucalyptus 15x, Hepar sulph. calc. 15x, Histaminum hydrochloricum 15x, Ipecac. 15x, Kali bic. 15x, Kali carb. 15x, Kali iod. 15x, Lycopodium 15x, Myrrha 15x, Nat. sulphuricum 15x, Nux vom. 15x, Phos. 15x, Pulsatilla 15x, Sanguinaria 15x, Spongia 15x, Stannum met. 15x, Tussilago far. 15x, Verbascum 15x, Influenzinum 30x.

OTC - PURPOSE SECTION

Formulated for symptoms such as excess mucus, cough, congestion and shortness of breath.

INACTIVE INGREDIENT SECTION

Inactive Ingredients: Gluten-free, non-GMO, organic beet-derived sucrose (lactose-free) pellets.

QUESTIONS SECTION

newtonlabs.net - Questions? 800.448.7256

Newton Laboratories, Inc. FDA Est # 1051203 Conyers, GA 30013

WARNINGS SECTION

WARNINGS: Keep out of reach of children. Do not use if tamper-evident seal is broken or missing. If symptoms worsen or persist for more than a few days, consult a doctor. If pregnant breast-feeding, ask a doctor before use.

OTC - PREGNANCY OR BREAST FEEDING SECTION

If pregnant or breast-feeding, ask a doctor before use.

OTC - KEEP OUT OF REACH OF CHILDREN SECTION

Keep out of reach of children.